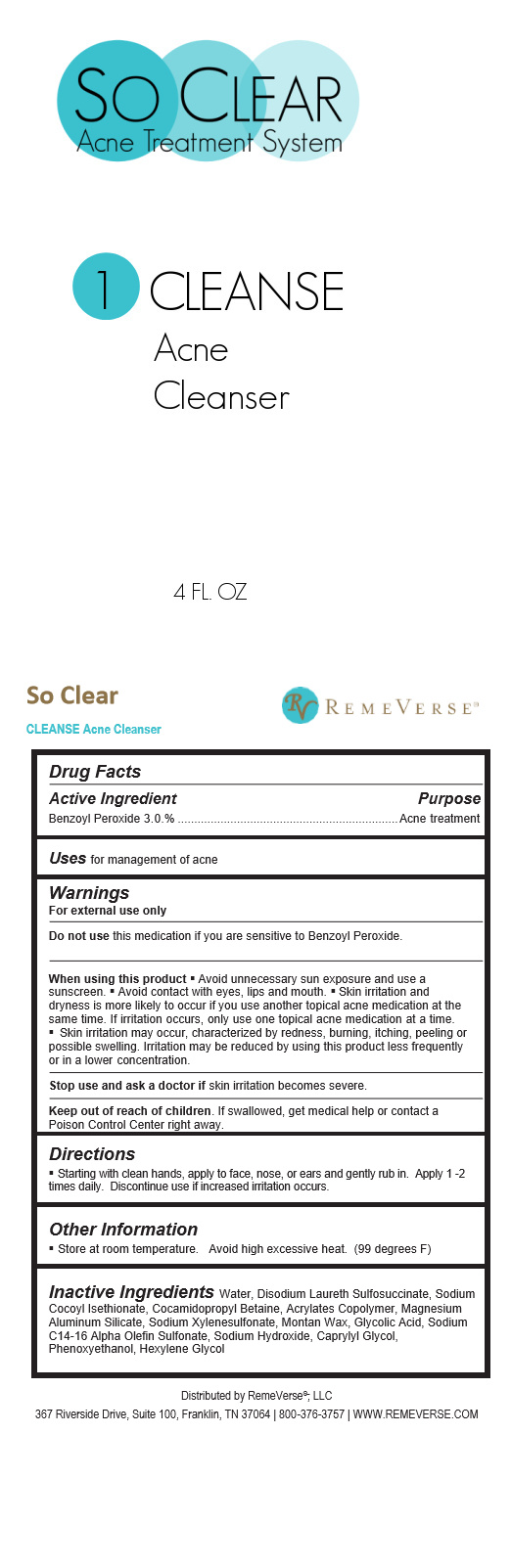 DRUG LABEL: So Clear Cleanse Acne Cleanser
NDC: 70317-146 | Form: LIQUID
Manufacturer: RemeVerse
Category: otc | Type: HUMAN OTC DRUG LABEL
Date: 20241216

ACTIVE INGREDIENTS: BENZOYL PEROXIDE 3.6 g/120 mL
INACTIVE INGREDIENTS: GLYCOLIC ACID; SODIUM XYLENESULFONATE; MONTAN WAX; ACRYLATES CROSSPOLYMER-6; DISODIUM LAURETH SULFOSUCCINATE; SODIUM COCOYL ISETHIONATE; SODIUM C14-16 OLEFIN SULFONATE; SODIUM HYDROXIDE; MAGNESIUM ALUMINUM SILICATE

So Clear Cleanse Acne Cleanser

So Clear Cleanse Acne Cleanser

Benzoyl Peroxide

So Clear Cleanse Acne Cleanser

Water, Disodium Laureth Sulfosuccinate, Sodium Cocoyl Isethionate, Cocamidopropyl Betaine, Acrylates Copolymer, Magnesium Aluminum Silicate, Sodium Xylenesulfonate, Montan Wax, Glycolic Acid, Sodium C14-16 Alpha Olefin Sulfonate, Sodium Hydroxide, Caprylyl Glycol, Phenoxyethanol, Hexylene Glycol

Directions

Starting with clean hands, apply to face, nose, or ears and gently rub in. Apply 1 -2 times daily. Discontinue use if increased irritation occurs.

Uses

for management of acne

Store at room temperature. Avoid high excessive heat. (99 degrees F)

Warnings

For external use only

Do not use this medication if you are sensitive to Benzoyl Peroxide.

When using this product § Avoid unnecessary sun exposure and use a sunscreen. § Avoid contact with eyes, lips and mouth. § Skin irritation and dryness is more likely to occur if you use another topical acne medication at the same time. If irritation occurs, only use one topical acne medication at a time.

Skin irritation may occur, characterized by redness, burning, itching, peeling or possible swelling. Irritation may be reduced by using this product less frequently or in a lower concentration.

Stop use and ask a doctor if skin irritation becomes severe.

Label

Deleted image of So Clear Cleanse label OTC drug panel (002).jpg and inserted new image of So Clear Cleanse label OTC drug panel (003).jpg So Clear Cleanse label OTC drug panel (003).jpg

This new label change is the name of product at the top of image to SO Clear Cleanse Acne Cleanser

Erased from WARNING SECTION "Keep out of reach of children. If swallowed, get medical help or contact a Poison Control Center right away." AND added same language removed to OTC - KEEP OUT OF REACHOF CHILDREN section.

Stop Use Section

Stop use and ask a doctor if skin irritation becomes severe.

So Clear Cleanse Acne Cleanser

Acne treatment

Keep out of the reach of Children

Keep out of reach of children. If swallowed, get medical help or contact a Poison Control Center right away.